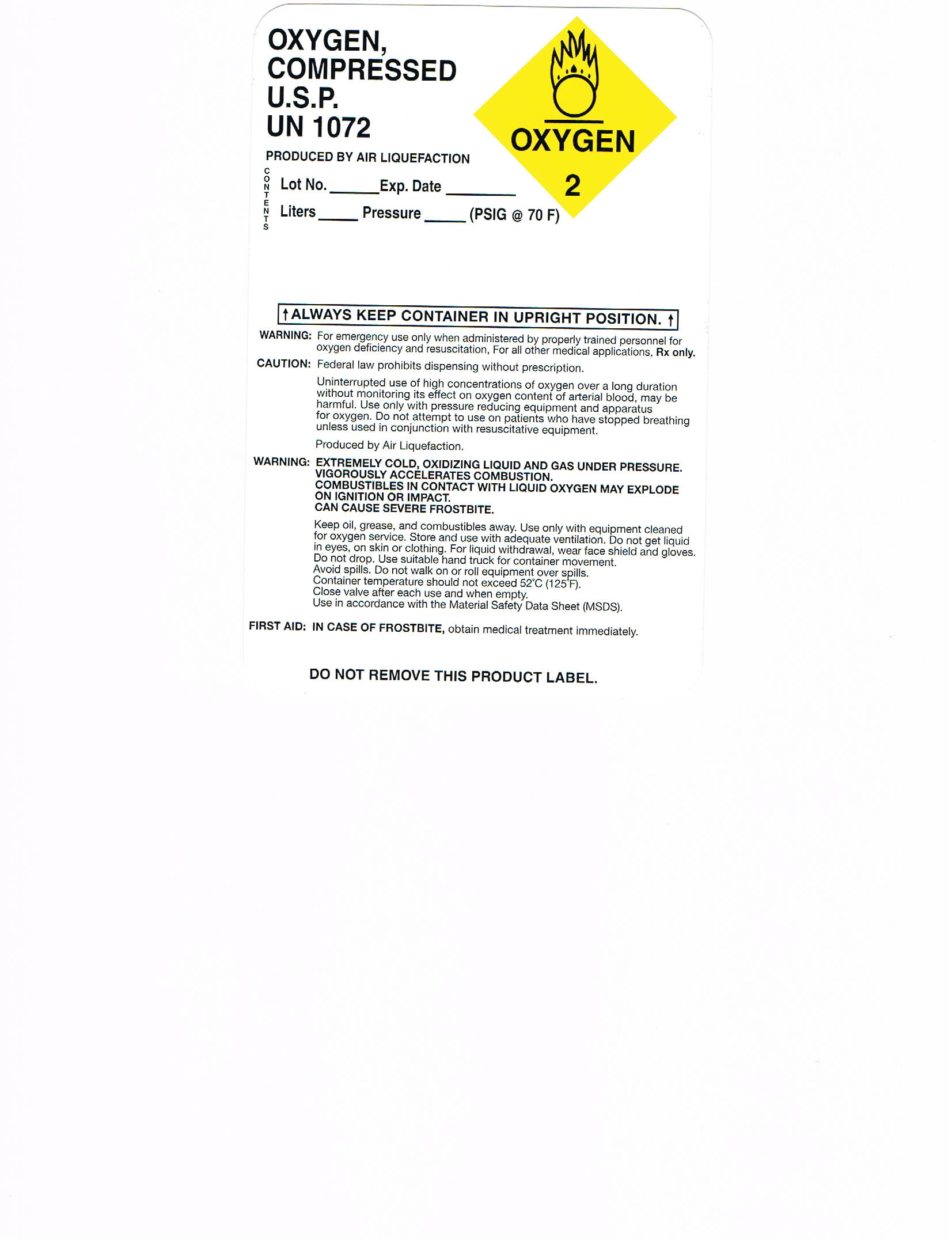 DRUG LABEL: OXYGEN
NDC: 10358-1417 | Form: GAS
Manufacturer: AIRSENSE INC
Category: prescription | Type: HUMAN PRESCRIPTION DRUG LABEL
Date: 20091120

ACTIVE INGREDIENTS: OXYGEN 995 mL/1 L

PACKAGE LABEL

MM1